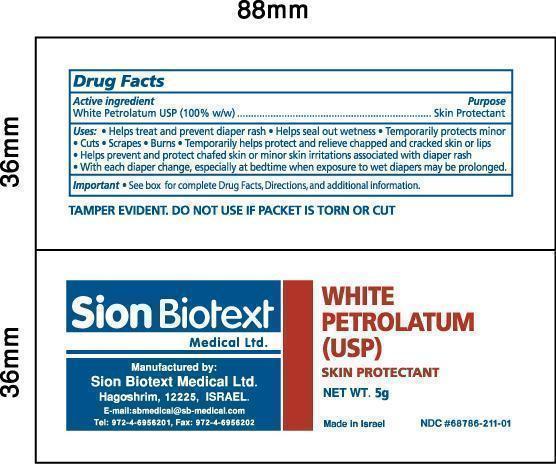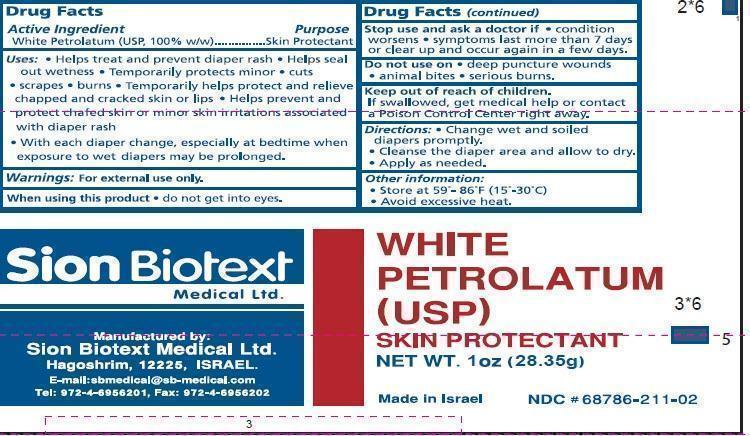 DRUG LABEL: WHITE PETROLATUM
NDC: 68786-211 | Form: JELLY
Manufacturer: Sion Biotext Medical Ltd
Category: otc | Type: HUMAN OTC DRUG LABEL
Date: 20260223

ACTIVE INGREDIENTS: PETROLATUM 1 g/1 g

Petrolatum Jelly

Active Ingredient

White Petrolatum (USP, 100% w/w)

Purpose

Skin Protectant

Uses:

- Helps treat and prevent diaper rash
- Helps seal out wetness
- Temporarily protects minor * cuts * scrapes * burns
- Temporarily helps protect and relieve chapped and cracked skin or lips
- Helps prevent and protect chafed skin or minor skin irritations associated with diaper rash
- With each diaper change, especially at bedtime when exposure to wet diapers may be prolonged.

Warnings:

For external use only.

When using this product

- do not get into eyes.

Stop use and ask a doctor if

- condition worsens
- symptoms last more than 7 days or clear up and occur again in a few days.

Do not use on

- deep puncture wounds
- animal bites
- serious burns.

Keep out of reach of children.

If swallowed, get medical help or contact a Poison Control Center right away.

Directions:

- Change wet and soiled diapers promptly.
- Cleanse the diaper area and allow to dry.
- Apply as needed.

Other Information

- Store at 59-86°F (15-30°C)
- Avoid excessive heat

Inactive Ingredients

None

Principal Display Panel

WHITE PETROLATUM (USP)

SKIN PROTECTANT

Made in Israel